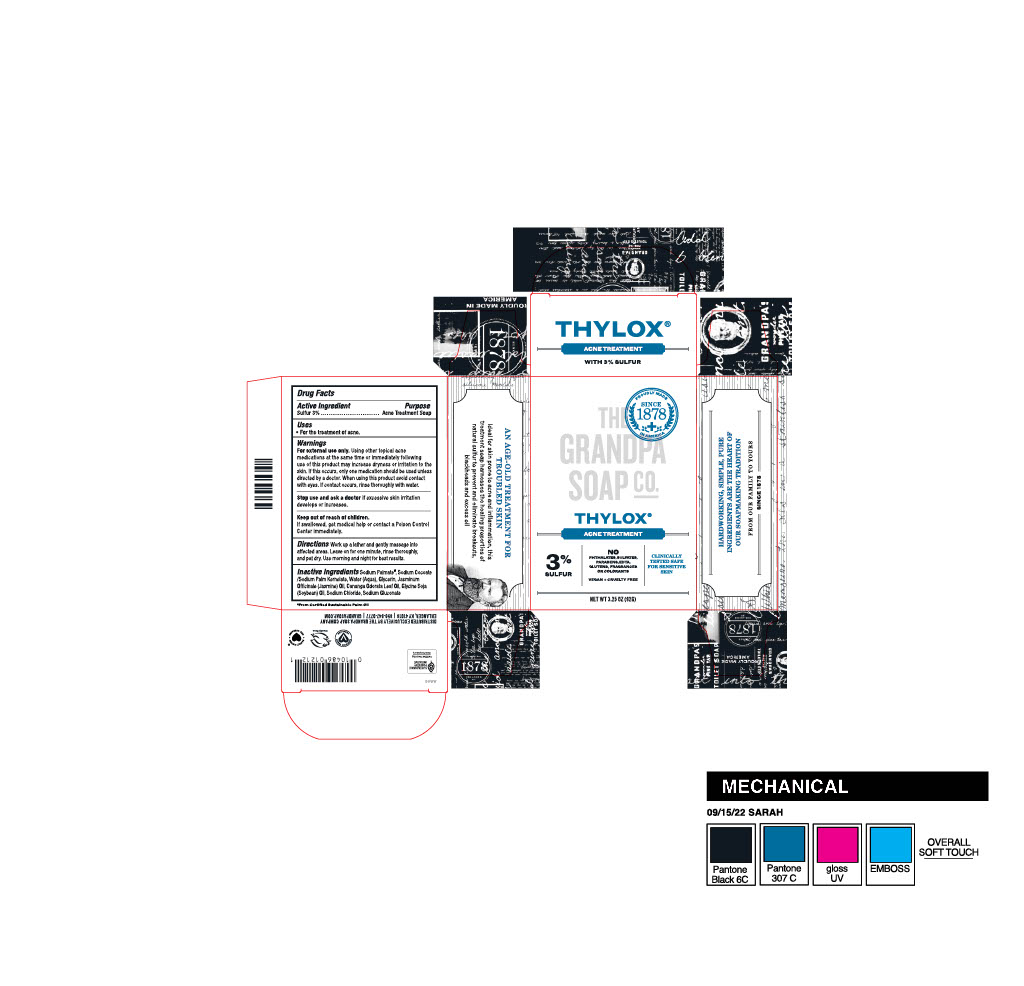 DRUG LABEL: THYLOX
NDC: 11118-1002 | Form: SOAP
Manufacturer: Bradford Soap Works, Inc.
Category: otc | Type: HUMAN OTC DRUG LABEL
Date: 20251231

ACTIVE INGREDIENTS: SULFUR 3 g/100 g
INACTIVE INGREDIENTS: SODIUM PALMATE; SODIUM COCOATE; SODIUM PALM KERNELATE; WATER; GLYCERIN; JASMINUM OFFICINALE FLOWER; CANANGA ODORATA LEAF OIL; SOYBEAN OIL; SODIUM CHLORIDE; SODIUM GLUCONATE

The Grandpa Soap Co. Thylox - 11118-1002

Drug Facts Active Ingredient

Sulfur 3%

Purpose

Acne Treatment Soap

Keep out of reach of children.

If swallowed, get medical help or contact a Poison Control Center immediately.

Uses

- For the treatment of acne.

Warnings

For external use only.

Using other topical acne medications at the same time or immediately following use of this product may increase dryness or irritation to the skin. If this occurs, only one medication should be used unless directed by a doctor. When using this product avoid contact with eyes. If contact occurs, rinse thoroughly with water.

Stop use and ask a doctor

if excessive skin irritation develops or increases.

Directions

Work up a lather and gently massage into affected areas. Leave on for one minute, rinse thoroughly, and pat dry. Use morning and night for best results.

Inactive Indredients

Sodium Palmate, Sodium Cocoate/Sodium Palm Kernelate, Water (Aqua), Glycerin, Jasminum Officinale (Jasmine) Oil, Cananga Odorata Leaf Oil, Glycine Soja (Soybean) Oil, Sodium Chloride, Sodium Gluconate

THE GRANDPA SOAP CO., THYLOX

THYLOX®

ALL NATURAL, 100% VEGETABLE BASE

ACNE TREATMENT

WITH 3% SULFUR

THE GRANDPA SOAP COMPANY